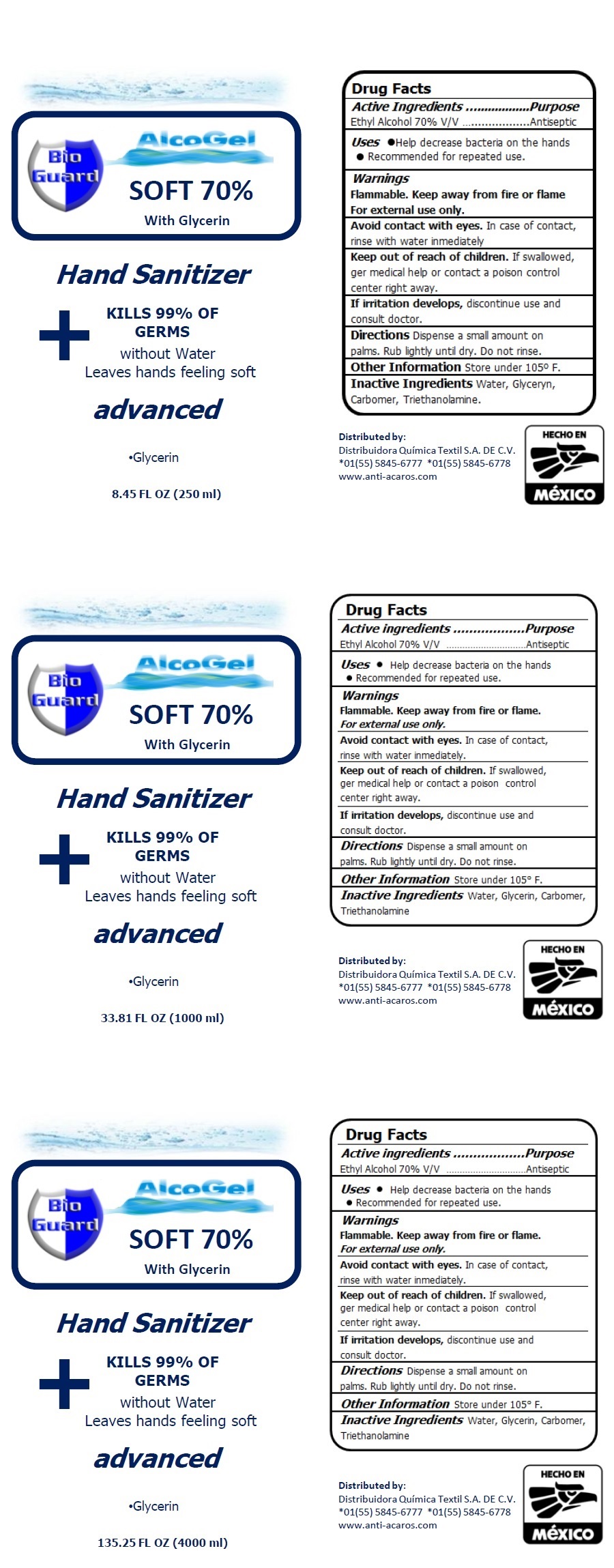 DRUG LABEL: ALCOGEL SOFT 70% Hand Sanitizer
NDC: 78978-001 | Form: GEL
Manufacturer: Distribuidora Quimica Textil, S.A. de C.V.
Category: otc | Type: HUMAN OTC DRUG LABEL
Date: 20200624

ACTIVE INGREDIENTS: ALCOHOL 70 mL/100 mL
INACTIVE INGREDIENTS: WATER; GLYCERIN; CARBOMER HOMOPOLYMER, UNSPECIFIED TYPE; TROLAMINE

Bio Guard AlcoGel Hand Sanitizer

Active Ingredients

Ethyl Alcohol 70% v/v

Purpose

Antiseptic

INDICATIONS AND USAGE

Uses • Help decrease bacteria on the hands

• Recommended for repeated use.

Warnings

Flammable. Keep away from fire or flame.

For external use only

Avoid contact with eyes. In case of contact, rinse with water immediately.

If irritation develops, discontinue use and consult doctor.

Keep out of reach of children. If swallowed, get medical help or contact a poison control center right away.

DOSAGE AND ADMINISTRATION

Directions Dispense a small amount on palms. Rub lightly until dry. Do not rinse.

Other Information Store under 105° F.

Inactive Ingredients Water, Glycerin, Carbomer, Triethanolamine

SOFT 70%

With Glycerin

KILLS 99% OF GERMS

without Water

Leaves hands feeling soft

advanced

Distributed by:

Distribuidora Quimica Textil, S.A. DE C.V.

*01(55) 5845-6777 *01(55) 5845-6778

www.anti-acaros.com